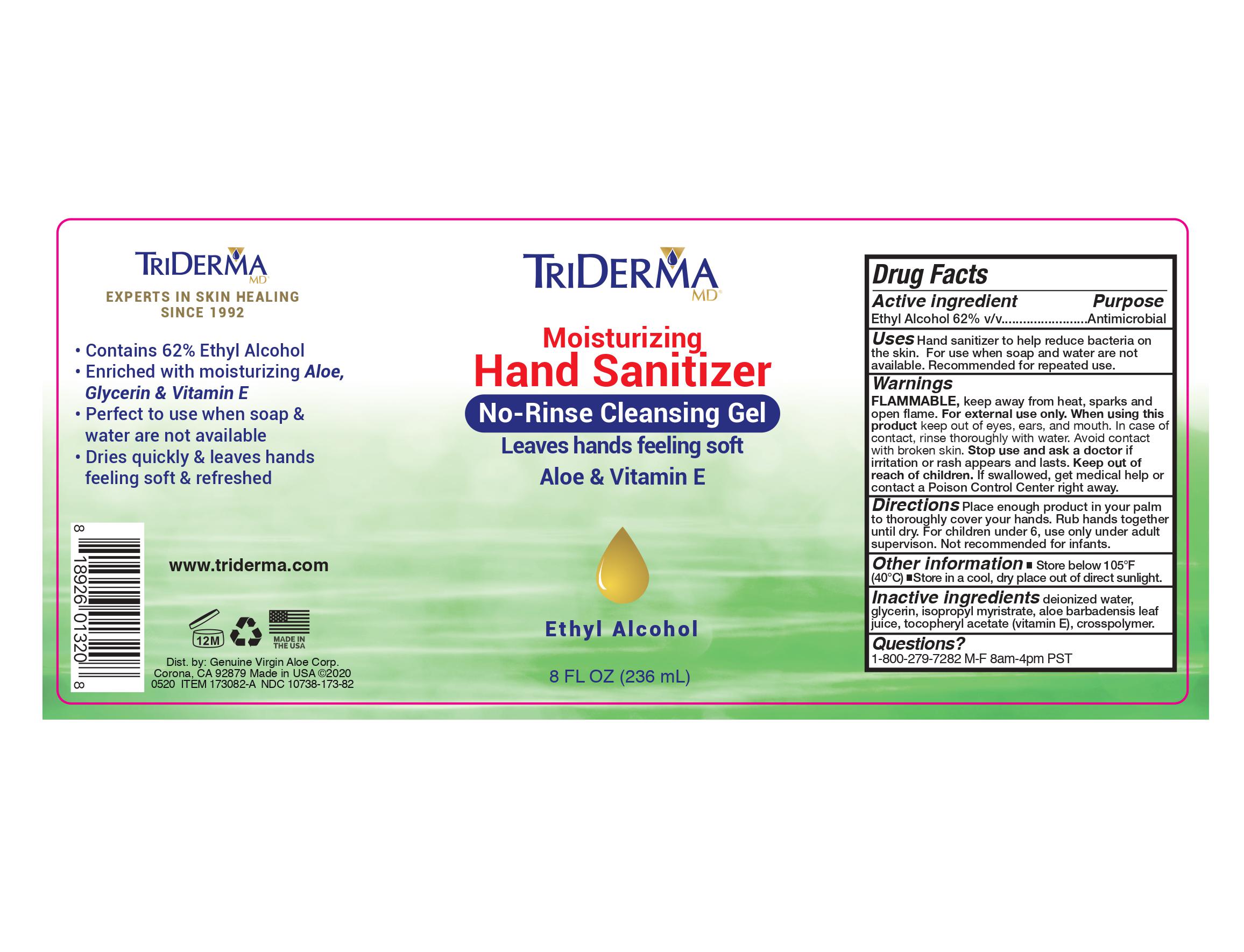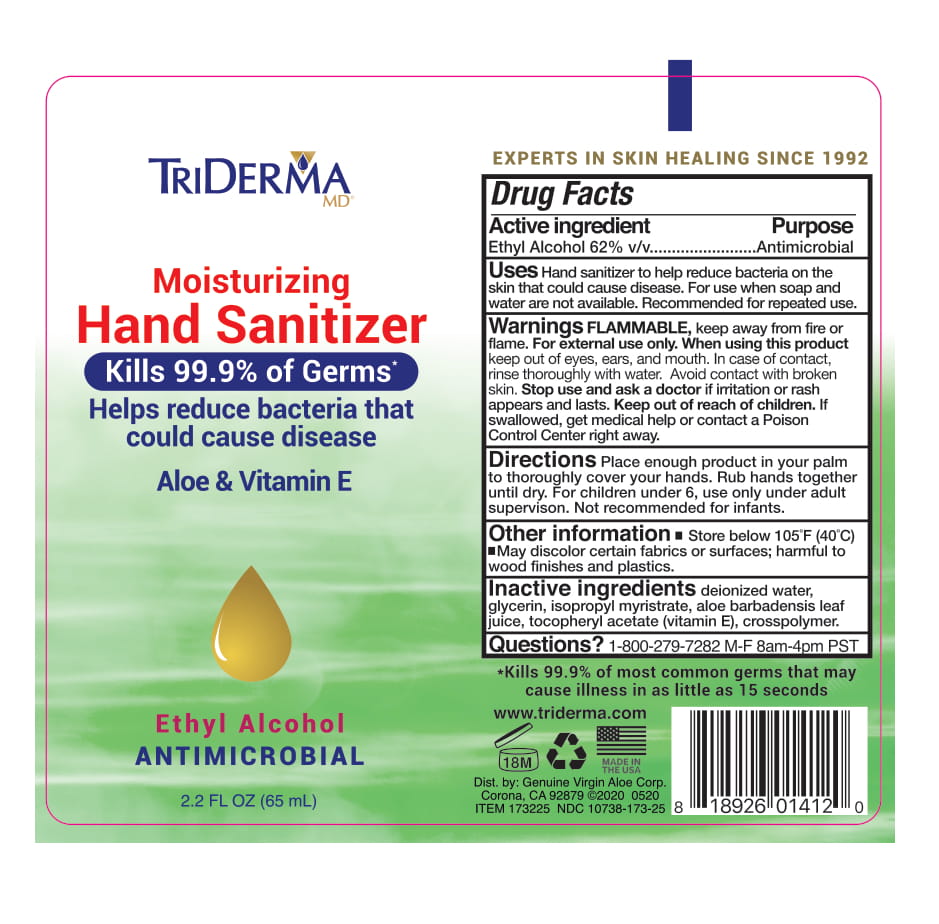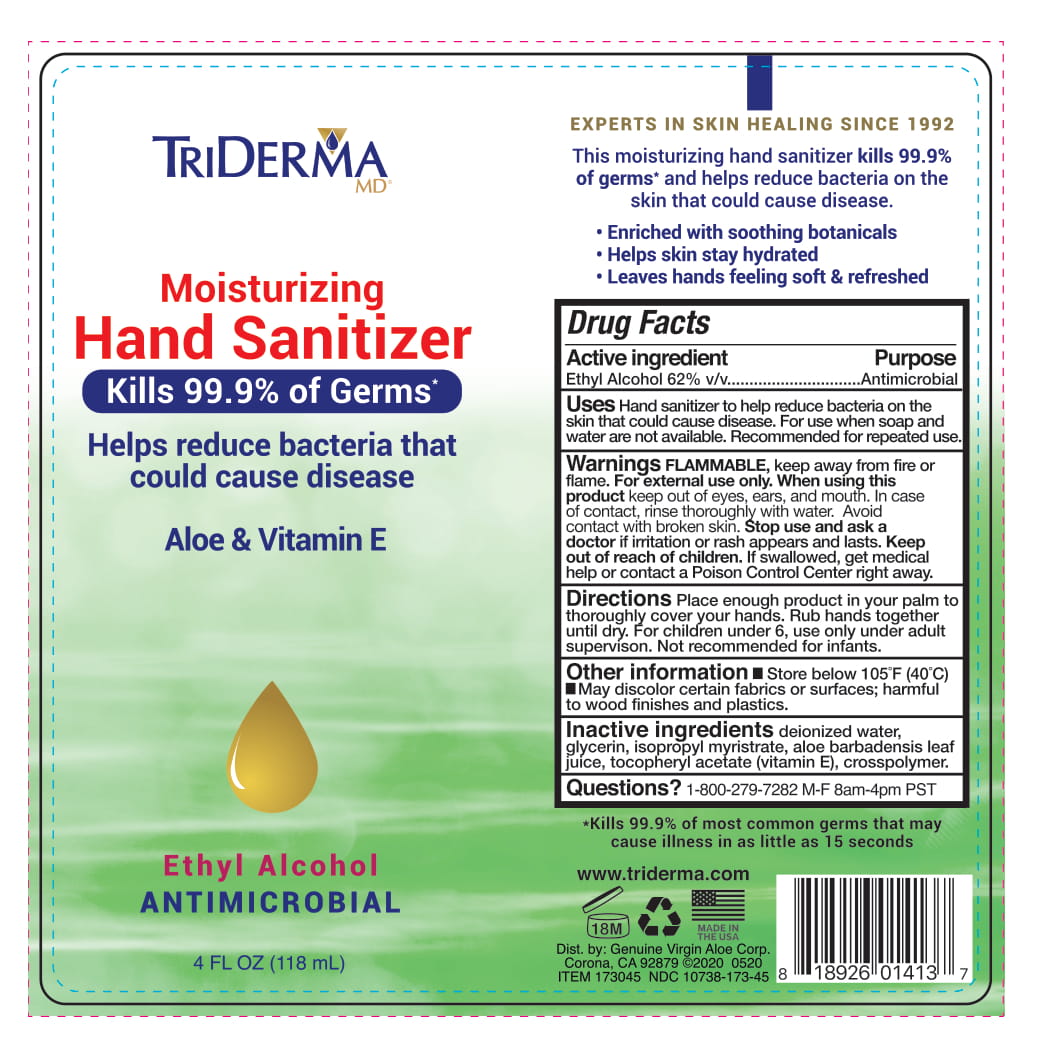 DRUG LABEL: Triderma Moisturizing Hand Sanitizer
NDC: 10738-173 | Form: GEL
Manufacturer: Genuine Virgin Aloe Corporation
Category: otc | Type: HUMAN OTC DRUG LABEL
Date: 20230202

ACTIVE INGREDIENTS: ALCOHOL 0.62 mL/1 mL
INACTIVE INGREDIENTS: ALOE VERA LEAF; GLYCERIN; ISOPROPYL MYRISTATE; WATER; .ALPHA.-TOCOPHEROL ACETATE, DL-

Triderma MD® Moisturizing Hand Sanitizer 62%

Active ingredient

Ethyl Alcohol 62% v/v

Purpose

Antimicrobial

Uses

Hand sanitizer to help reduce bacteria on the skin that could cause disease. For use when soap and water are not available. Recommended for repeated use.

NDC 10738-173-82

Hand sanitizer to help reduce bacteria on the skin. For use when soap and water are not available. Recommended for repeated use.

Warnings

Flammable, keep away from fire or flame.

For external use only

When using this product

keep out of eyes, ears and mouth. In case of contact rinse thoroughly with water. Avoid contact with broken skin.

Stop use and ask a doctor

if irritation or rash appears and lasts.

Keep out of reach of children.

If swallowed, get medical help or contact a Poison Control Center right away.

Directions

Place enough product in your palm to thoroughly cover your hands. Rub hands together until dry. For children under 6, use only under adult supervision. Not recommended for infants.

Other information

- Store below 105° F (40° C)
- May discolor certain fabrics or surfaces; harmful to wood finishes and plastics.

Inactive ingredients

deionized water, glycerin, isopropyl myristrate, aloe barbadensis leaf juice, tocopheryl acetate (vitamin E), crosspolymer

Questions?

1-800-279-7282 M-F 8am-4pm PST

Labels

2.2 fl. oz. (65 ml) - NDC 10738-173-25

Triderma MD®

Moisturizing Hand Sanitizer

Kills 99% of Germs*

Helps reduce bacteria that could cause disease

Aloe & Vitamin E

Ethyl Alcohol

ANTIMICROBIAL

EXPERTS IN SKIN HEALING SINCE 1992

*Kills 99.9% of most common germs that may cause illness in as little as 15 seconds

Triderma.com

Dist. by: Genuine Virgin Aloe Corp.

Corona, CA 92879 ©2020

ITEM 173225 NDC 10738-173-25

4 fl. oz. (118 ml) - NDC 10738-173-45

Triderma MD®

Moisturizing Hand Sanitizer

Kills 99% of Germs*

Helps reduce bacteria that could cause disease

Aloe & Vitamin E

Ethyl Alcohol

ANTIMICROBIAL

EXPERTS IN SKIN HEALING SINCE 1992

*Kills 99.9% of most common germs that may cause illness in as little as 15 seconds

Triderma.com

Dist. by: Genuine Virgin Aloe Corp.

Corona, CA 92879 ©2020

ITEM 173045 NDC 10738-173-45

8 fl. oz. (236 ml) - NDC 10738-173-82

Triderma MD®

Moisturizing Hand Sanitizer

Leaves hands Feeling Soft

Aloe & Vitamin E

Ethyl Alcohol

ANTIMICROBIAL

EXPERTS IN SKIN HEALING SINCE 1992

• Contains 62% Ethyl Alcohol • Enriched with moisturizing Aloe, Glycerin & Vitamin E

• Perfect to use when soap & water are not available

• Dries quickly & leaves hands feeling soft & refreshed

Triderma.com

Dist. by: Genuine Virgin Aloe Corp.

Corona, CA 92879 ©2020

ITEM 173082-A NDC 10738-173-82